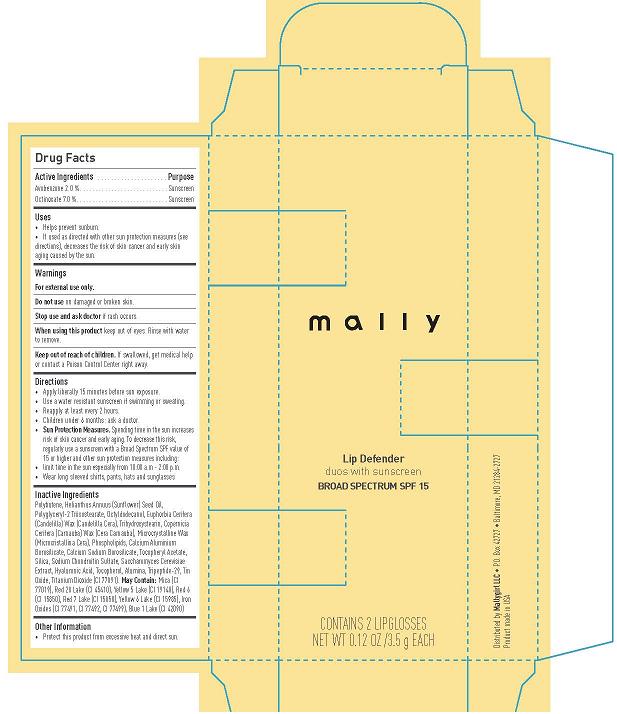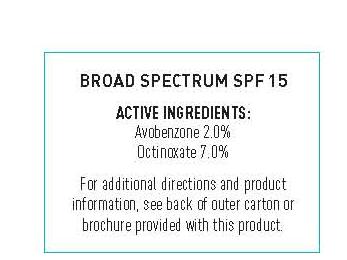 DRUG LABEL: mally Lip Defender
NDC: 76119-5310 | Form: GEL
Manufacturer: MallyGirl, LLC
Category: otc | Type: HUMAN OTC DRUG LABEL
Date: 20120501

ACTIVE INGREDIENTS: AVOBENZONE 0.07 g/3.5 g; OCTINOXATE .245 g/3.5 g
INACTIVE INGREDIENTS: POLYBUTENE (1400 MW); SUNFLOWER OIL; OCTYLDECANOL; CANDELILLA WAX; TRIHYDROXYSTEARIN; CARNAUBA WAX; MICROCRYSTALLINE WAX; .ALPHA.-TOCOPHEROL ACETATE; SILICON DIOXIDE; SODIUM CHONDROITIN SULFATE (PORCINE; 5500 MW); SACCHAROMYCES CEREVISIAE; HYALURONIC ACID; TOCOPHEROL; ALUMINUM OXIDE; STANNIC OXIDE; TITANIUM DIOXIDE; MICA; D&C RED NO. 28; FD&C YELLOW NO. 5; D&C RED NO. 6; D&C RED NO. 7; FD&C YELLOW NO. 6; FERRIC OXIDE RED; FD&C BLUE NO. 1

mally Lip Defender - Conquering Red - Broad Spectrum SPF 15

Active Ingredients

Avobenzone 2.0%

Octinoxate 7.0%

Purpose

Sunscreen

Sunscreen

Use

- Helps prevent sunburn.
- If used as directed with other sun protection measures (see directions), decreases the risk of skin cancer and early skin aging caused by the sun.

WARNINGS

For external use only

Do not use on damaged or broken skin.

Stop use and ask doctor if rash occurs.

When using this product keep out of eyes. Rinse with water to remove.

Keep out of reach of children. If swollowed, get medical help or contact a Poison Control Center right away.

Directions

- Apply liberally 15 minutes before sun exposure.
- Use a water resistant sunscreen if swimming or sweating.
- Reapply at least every 2 hours.
- Children under 6 months: ask a doctor.
- Sun Protection Measures. Spending time in the sun increases risk of skin cancer and early aging. To decrease this risk regularly use a sunscreen with a Broad Spectrum SPF value of 15 or higer and other sun protection measures including:
- Limit time in the sun especially from 10:00 a.m. - 2:00 p.m.
- Wear long sleeved shirts, pants, hats and sunglasses

Inactive Ingredients

Polybutene, Helianthus annuus (sunflower) seed oil, Polyglyceryl-2 triisostearate, Octyldecanol, Euphorbia cerifera (candelilla) wax (candelilla cera), Trihydroxystearin, Copernicia cerifera (carnauba) wax (cera carnauba), Microcrystalline wax (microcristallina cera), Phospholipids, Calcium aluminum borosilicate, Calcium sodium borosilicate, Tocopheryl acetate, Silica, Sodium chondroitin sulfate, Saccharomyces cerevisiae extract, Hyaluronic acid, Tocopherol, Alumina, Tripeptide-29, Tin oxide, Titanium dioxide (CI 77891) May Contain: Mica (CI 77019), Red 28 Lake (CI 45410), Yellow 5 Lake (CI 19140), Red 6 (CI 15850), Red 7 Lake (CI 15850), Yellow 6 Lake (CI 15985), Iron Oxides (CI 77491, CI 77492, CI 77499), Blue 1 Lake (CI 42090)

Other Information

- Protect this product from excessive heat and direct sun.

Principal Display Panel

mally

Lip Defender
Conquering Red
duos with sunscreen
Broad Spectrum SPF 15